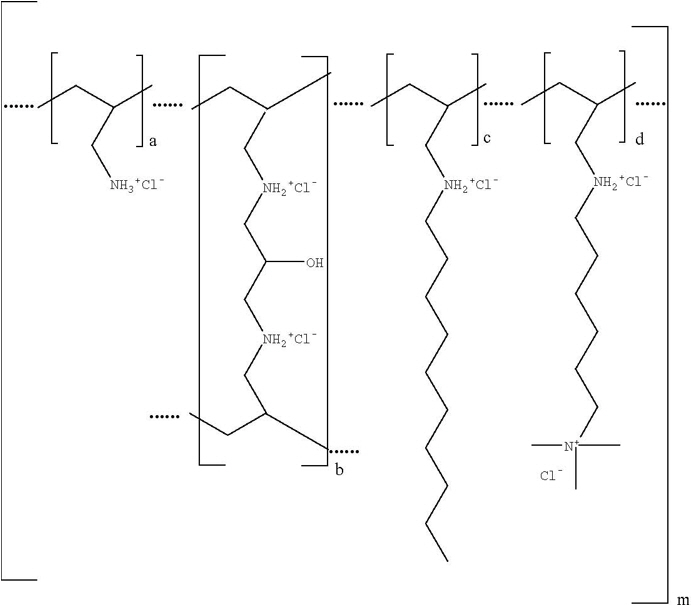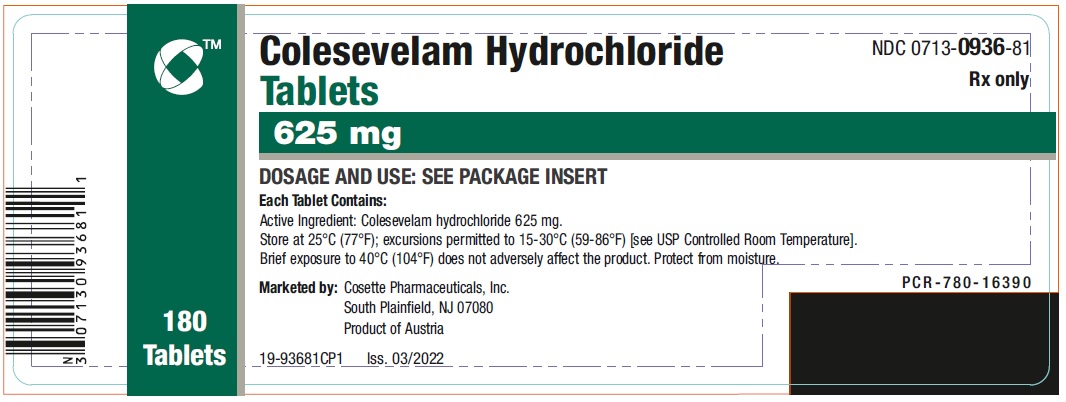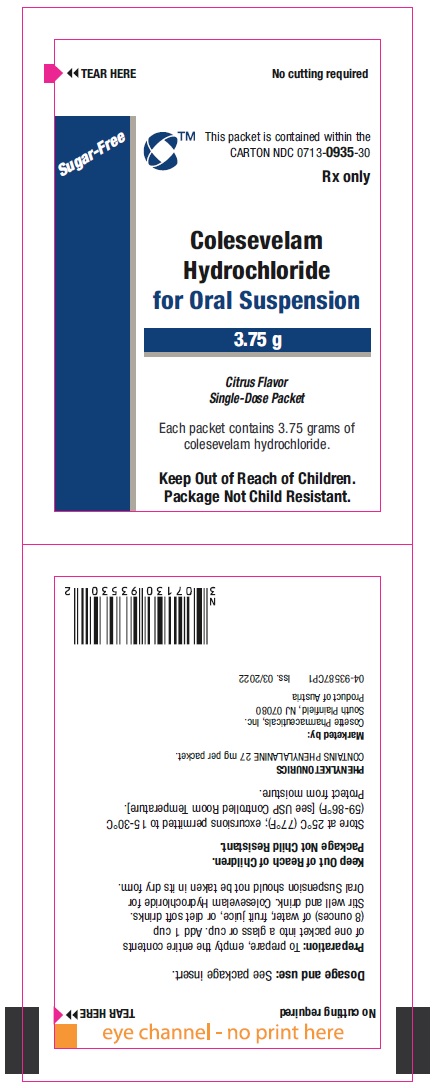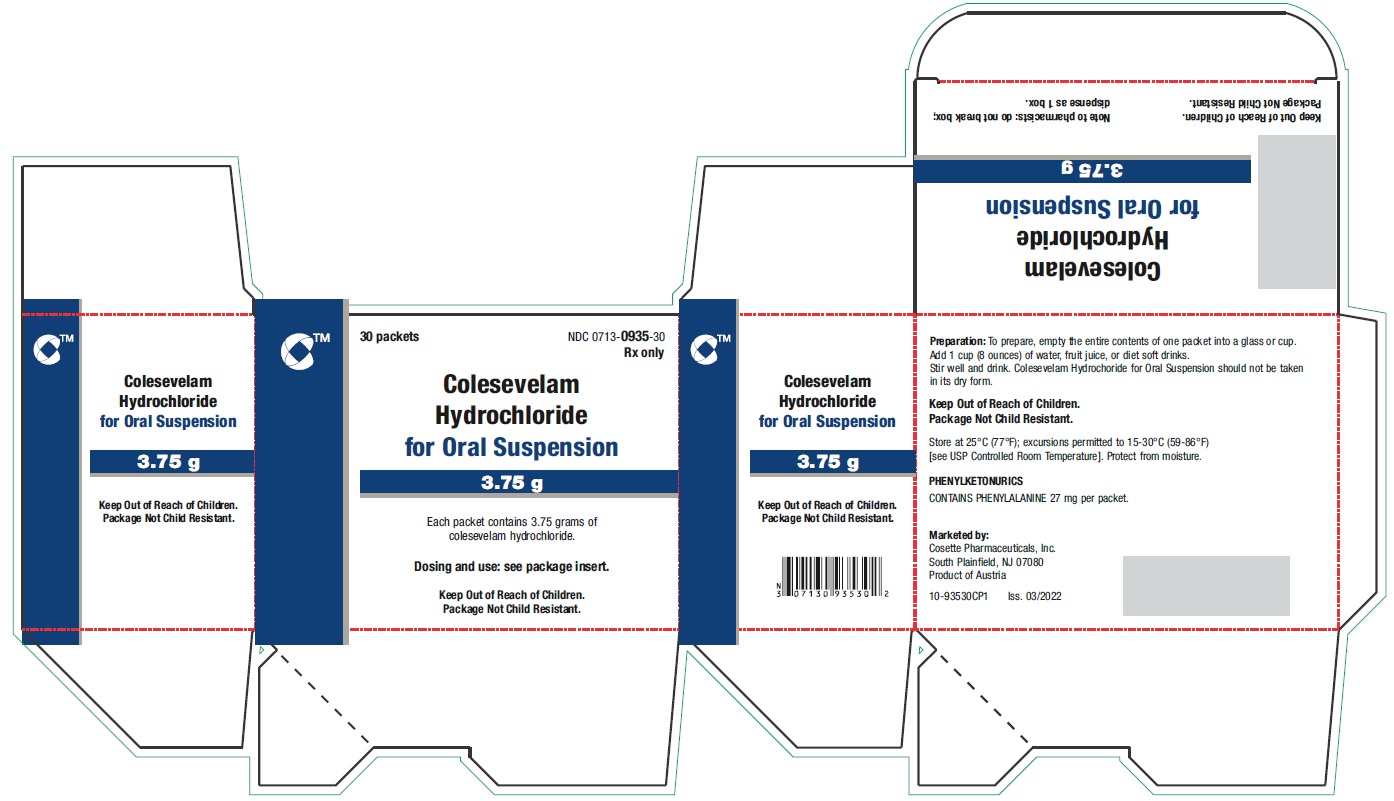 DRUG LABEL: COLESEVELAM HYDROCHLORIDE
NDC: 0713-0936 | Form: TABLET, FILM COATED
Manufacturer: Cosette Pharmaceuticals, Inc.
Category: prescription | Type: HUMAN PRESCRIPTION DRUG LABEL
Date: 20241226

ACTIVE INGREDIENTS: COLESEVELAM HYDROCHLORIDE 625 mg/1 1
INACTIVE INGREDIENTS: MAGNESIUM STEARATE; MICROCRYSTALLINE CELLULOSE; SILICON DIOXIDE; HYPROMELLOSE, UNSPECIFIED

HIGHLIGHTS OF PRESCRIBING INFORMATION

These highlights do not include all the information needed to use COLESEVELAM HYDROCHLORIDE safely and effectively. See full prescribing information for COLESEVELAM HYDROCHLORIDE.
COLESEVELAM HYDROCHLORIDE tablets, for oral use
COLESEVELAM HYDROCHLORIDE for oral suspension
Initial U.S. Approval: 2000

1 INDICATIONS AND USAGE

Colesevelam hydrochloride is a bile acid sequestrant indicated as an adjunct to diet and exercise to:

- reduce elevated low-density lipoprotein cholesterol (LDL-C) in adults with primary hyperlipidemia (1.1).
- reduce LDL-C levels in boys and postmenarchal girls, 10 to 17 years of age, with heterozygous familial hypercholesterolemia (HeFH), unable to reach LDL-C target levels despite an adequate trial of diet and lifestyle modification (1.1).
- improve glycemic control in adults with type 2 diabetes mellitus (1.2).

Limitations of Use (1.3):

- Do not use for treatment of type 1 diabetes or for diabetic ketoacidosis.
- Not studied in Fredrickson Type I, III, IV, and V dyslipidemias

2 DOSAGE AND ADMINISTRATION

- Obtain lipid parameters, including serum triglyceride (TG) levels, before starting colesevelam hydrochloride (2.1).
- The recommended dosage for adults and for boys and postmenarchal girls aged 10 to 17 years with primary hyperlipidemia is 3.75 grams daily. The recommended dosage for adults with type 2 diabetes mellitus is 3.75 grams daily. Colesevelam hydrochloride should be taken as follows (2.2, 2.4):

Tablets

Take 6 tablets once daily or 3 tablets twice daily with a meal and liquid.

For Oral Suspension

Take one packet once daily with a meal. To prepare, empty the entire contents of one packet into a glass or cup. Add 1 cup of water, fruit juice, or diet soft drinks. Stir well and drink.

3 DOSAGE FORMS AND STRENGTHS

- Tablets: 625 mg (3)
- For Oral Suspension: 3.75 gram packet (3)

4 CONTRAINDICATIONS

- Patients with serum triglyceride levels >500 mg/dL (4)
- Patients with a history of hypertriglyceridemia-induced pancreatitis (4)
- Patients with a history of bowel obstruction (4)

5 WARNINGS AND PRECAUTIONS

- Hypertriglyceridemia and Pancreatitis: Colesevelam hydrochloride can increase TG. Hypertriglyceridemia can cause acute pancreatitis. Monitor lipids, including TG. Instruct patients to discontinue colesevelam hydrochloride and seek prompt medical attention if the symptoms of acute pancreatitis occur (5.1).
- Gastrointestinal Obstruction:Cases of bowel obstruction have occurred. Colesevelam hydrochloride is not recommended in patients with gastroparesis, other gastrointestinal motility disorders, and in those who have had major gastrointestinal tract surgery and who may be at risk for bowel obstruction (5.2).
- Vitamin K or Fat-Soluble Vitamin Deficiencies: Colesevelam hydrochloride may decrease absorption of fat-soluble vitamins. Patients with a susceptibility to deficiencies of vitamin K (e.g., patients on warfarin, patients with malabsorption syndromes) or other fat-soluble vitamins may be at increased risk. Patients on oral vitamin supplementation should take their vitamins at least 4 hours prior to colesevelam hydrochloride (5.3).
- Drug Interactions:Due to the potential for decreased absorption of other drugs that have not been tested for interaction, consider administering at least 4 hours prior to colesevelam hydrochloride (5.4, 7, 12.3).
- Risks in Patients with Phenylketonuria (PKU):Phenylalanine can be harmful to patients with phenylketonuria. Colesevelam hydrochloride for oral suspension contains 27 mg phenylalanine per 3.75 gram packet (5.5, 11).

6 ADVERSE REACTIONS

In clinical trials, the most common (incidence ≥2% and greater than placebo) adverse reactions with colesevelam hydrochloride included constipation, dyspepsia, and nausea (6.1).

To report SUSPECTED ADVERSE REACTIONS, contact Cosette Pharmaceuticals, Inc. at 1-800-922-1038 or FDA at 1-800-FDA-1088 or www.fda.gov/medwatch.

7 DRUG INTERACTIONS

Concomitant use with colesevelam hydrochloride may decrease the exposure of the following drugs:Drugs with a narrow therapeutic index (e.g., cyclosporine), phenytoin, thyroid hormone replacement therapy, warfarin, oral contraceptives containing ethinyl estradiol and norethindrone, olmesartan medoxomil, and sulfonylureas (glimepiride, glipizide, glyburide). Administer these drugs 4 hours prior to colesevelam hydrochloride. For patients on warfarin, monitor International Normalized Ratio (INR) frequently during initiation then periodically (7.1).

Concomitant use with colesevelam hydrochloride may increase the exposure of the following drugs:Metformin extended release. Monitor patients' glycemic control (7.2).

FULL PRESCRIBING INFORMATION

1 INDICATIONS AND USAGE

1.1 Primary Hyperlipidemia

Colesevelam hydrochloride is indicated as an adjunct to diet and exercise to reduce elevated low-density lipoprotein cholesterol (LDL-C) in adults with primary hyperlipidemia.

Colesevelam hydrochloride is indicated to reduce LDL-C levels in boys and postmenarchal girls, 10 to 17 years of age, with heterozygous familial hypercholesterolemia (HeFH) who are unable to reach LDL-C target levels despite an adequate trial of dietary therapy and lifestyle modification.

1.2 Type 2 Diabetes Mellitus

Colesevelam hydrochloride is indicated as an adjunct to diet and exercise to improve glycemic control in adults with type 2 diabetes mellitus .

1.3 Limitations of Use

- Colesevelam hydrochloride should not be used for the treatment of type 1 diabetes or for the treatment of diabetic ketoacidosis.
- Colesevelam hydrochloride has not been studied in Fredrickson Type I, III, IV, and V dyslipidemias.

2 DOSAGE AND ADMINISTRATION

2.1 Testing Prior to Initiation of Colesevelam Hydrochloride

Obtain lipid parameters, including triglyceride (TG) levels, before starting colesevelam hydrochloride. Colesevelam hydrochloride is contraindicated in patients with TG levels >500 mg/dL [see Contraindications (4)and Warnings and Precautions (5.1)] .

2.2 Recommended Dosage in Primary Hyperlipidemia and Type 2 Diabetes Mellitus

The recommended dosage of colesevelam hydrochloride for adults and for boys and postmenarchal girls aged 10 to 17 years with primary hyperlipidemia is 3.75 grams daily. The recommended dosage of colesevelam hydrochloride for adults with type 2 diabetes mellitus is 3.75 grams daily. Colesevelam hydrochloride should be taken as follows:

Tablets

Take 6 tablets once daily or 3 tablets twice daily. Due to tablet size, colesevelam hydrochloride for oral suspension is recommended for use in the pediatric population.

For Oral Suspension

Take one packet once daily.

2.3 Important Dosing Information for Primary Hyperlipidemia

Colesevelam hydrochloride can be dosed at the same time as a statin, or colesevelam hydrochloride and the statin can be dosed apart .Monitor lipid levels within 4 to 6 weeks after initiation of colesevelam hydrochloride.

2.4 Administration Instructions

Tablets

Take colesevelam hydrochloride tablets with a meal and liquid. For patients with difficulty swallowing tablets, use colesevelam hydrochloride for oral suspension [see Warnings and Precautions (5.2)].

For Oral Suspension

To prepare, empty the entire contents of one packet into a glass or cup. Add 1 cup (8 ounces) of water, fruit juice, or diet soft drinks. Stir well and drink. Take colesevelam hydrochloride oral suspension with meals. Do not take colesevelam hydrochloride oral suspension in its dry form. Due to tablet size, colesevelam hydrochloride for oral suspension is recommended for use in the pediatric population.

3 DOSAGE FORMS AND STRENGTHS

- Tablets: 625 mg tablets are off-white, oval, film-coated and imprinted with "Sankyo" and "C01" on one side.
- For Oral Suspension: 3.75 gram packet containing a white to pale yellow powder with yellow granules.

4 CONTRAINDICATIONS

Colesevelam hydrochloride is contraindicated in patients with:

- Serum TG concentrations >500 mg/dL [see Warnings and Precautions (5.1)]
- History of hypertriglyceridemia-induced pancreatitis [see Warnings and Precautions (5.1)]
- A history of bowel obstruction [see Warnings and Precautions (5.2)]

5 WARNINGS AND PRECAUTIONS

5.1 Hypertriglyceridemia and Pancreatitis

Colesevelam hydrochloride, like other bile acid sequestrants, can increase serum TG concentrations. Hypertriglyceridemia can cause acute pancreatitis.

Colesevelam hydrochloride had effects on serum TG (median increase 5% compared to placebo) in trials of patients with primary hyperlipidemia.

In trials in patients with type 2 diabetes, greater increases in TG levels occurred when colesevelam hydrochloride was used as monotherapy (median increase 9.7% compared to placebo) and when colesevelam hydrochloride was used in combination with pioglitazone (median increase 11% compared to placebo in combination with pioglitazone), sulfonylureas (median increase 18% compared to placebo in combination with sulfonylureas), and insulin (median increase 22% compared to placebo in combination with insulin) [see Adverse Reactions (6.1)].

Obtain lipid parameters, including TG levels, before starting colesevelam hydrochloride and periodically thereafter. Colesevelam hydrochloride is contraindicated in patients with TG levels >500 mg/dL or patients with a history of hypertriglyceridemia-induced pancreatitis [see Contraindications (4)] . Patients with TG levels greater than 300 mg/dL could have greater increases in serum TG levels with colesevelam hydrochloride and may require additional TG monitoring. Instruct patients to discontinue colesevelam hydrochloride and seek prompt medical attention if the symptoms of acute pancreatitis occur (e.g., severe abdominal pain with or without nausea and vomiting). Discontinue colesevelam hydrochloride if TG levels exceed 500 mg/dL [see Adverse Reactions (6.1)] .

5.2 Gastrointestinal Obstruction

Postmarketing cases of bowel obstruction have occurred with colesevelam hydrochloride [see Adverse Reactions (6.2)] . Because of its constipating effects, colesevelam hydrochloride is not recommended in patients with gastroparesis, other gastrointestinal motility disorders, and in those who have had major gastrointestinal tract surgery and who may be at risk for bowel obstruction. Colesevelam hydrochloride is contraindicated in patients with a history of bowel obstruction [see Contraindications (4)] . Instruct patients to promptly discontinue colesevelam hydrochloride and seek medical attention if severe abdominal pain or severe constipation occurs.

Because of the tablet size, colesevelam hydrochloride tablets can cause dysphagia or esophageal obstruction. For patients with difficulty swallowing tablets, use colesevelam hydrochloride for oral suspension.

5.3 Vitamin K or Fat-Soluble Vitamin Deficiencies

Colesevelam hydrochloride may decrease the absorption of fat-soluble vitamins A, D, E, and K. Patients with a susceptibility to deficiencies of vitamin K (e.g., patients on warfarin, patients with malabsorption syndromes) or other fat-soluble vitamins may be at increased risk when taking colesevelam hydrochloride.

Patients on oral vitamin supplementation should take their vitamins at least 4 hours prior to colesevelam hydrochloride [see Drug Interactions (7.1)].

5.4 Drug Interactions

Colesevelam hydrochloride reduces gastrointestinal absorption of some drugs. Administer drugs with a known interaction at least 4 hours prior to colesevelam hydrochloride [see Drug Interactions (7)] .

Due to the potential for decreased absorption of other drugs that have not been tested for interaction, especially those with a narrow therapeutic index, consider administering at least 4 hours prior to colesevelam hydrochloride [see Clinical Pharmacology (12.3)].

5.5 Risks in Patients with Phenylketonuria (PKU)

Phenylalanine can be harmful to patients with PKU. Colesevelam hydrochloride for oral suspension contains phenylalanine, a component of aspartame. Each 3.75 gram packet contains 27 mg of phenylalanine. Before prescribing colesevelam hydrochloride for oral suspension to a patient with PKU, consider the combined daily amount of phenylalanine from all sources, including colesevelam hydrochloride for oral suspension.

6 ADVERSE REACTIONS

The following important adverse reactions are described below and elsewhere in the labeling:

- Hypertriglyceridemia and Pancreatitis [see Warnings and Precautions (5.1)]
- Gastrointestinal Obstruction [see Warnings and Precautions (5.2)]
- Vitamin K or Fat-Soluble Vitamin Deficiencies [see Warnings and Precautions (5.3)]

6.1 Clinical Studies Experience

Because clinical studies are conducted under widely varying conditions, adverse reaction rates observed in the clinical studies of a drug cannot be directly compared to rates in clinical studies of another drug and may not reflect the rates observed in practice.

Primary Hyperlipidemia

In 7 double-blind, placebo-controlled clinical trials, 807 patients with primary hyperlipidemia (age range 18-86 years, 50% women, 90% Caucasians, 7% Blacks, 2% Hispanics, 1% Asians) and elevated LDL-C were treated with colesevelam hydrochloride 1.5 g/day to 4.5 g/day from 4 to 24 weeks (total exposure 199 patient-years).

Table 1 Clinical Studies of Colesevelam Hydrochloride for Primary Hyperlipidemia: Adverse Reactions Reported in ≥ 2% of Patients and More Commonly than in Placebo
 | Colesevelam Hydrochloride N=807 | Placebo N=258
Constipation | 11.0% | 7.0%
Dyspepsia | 8.3% | 3.5%
Nausea | 4.2% | 3.9%
Accidental injury | 3.7% | 2.7%
Asthenia | 3.6% | 1.9%
Pharyngitis | 3.2% | 1.9%
Flu syndrome | 3.2% | 3.1%
Rhinitis | 3.2% | 3.1%
Myalgia | 2.1% | 0.4%

Pediatric Patients 10 to 17 Years of Age

In an 8-week double-blind, placebo-controlled study, boys and post-menarchal girls, 10 to 17 years of age, with HeFH (n=194), were treated with colesevelam hydrochloride tablets (1.9-3.8 g, daily) or placebo tablets.

Table 2 Clinical Study of Colesevelam Hydrochloride for Primary Hyperlipidemia in HeFH Pediatric Patients: Adverse Reactions Reported in ≥2% of Patients and More Commonly than in Placebo
 | Colesevelam Hydrochloride N=129 | Placebo N=65
Nasopharyngitis | 6.2% | 4.6%
Headache | 3.9% | 3.1%
Fatigue | 3.9% | 1.5%
Creatine Phosphokinase Increase | 2.3% | 0.0%
Rhinitis | 2.3% | 0.0%
Vomiting | 2.3% | 1.5%

The reported adverse reactions during the additional 18-week open-label treatment period with colesevelam hydrochloride 3.8 g per day were similar to those during the double-blind period and included headache (7.6%), nasopharyngitis (5.4%), upper respiratory tract infection (4.9%), influenza (3.8%), and nausea (3.8%).

Type 2 Diabetes Mellitus

In 5 add-on combination and 1 monotherapy double-blind, 12- to 26-week, placebo-controlled clinical trials in patients with type 2 diabetes mellitus, 1022 patients were treated with colesevelam hydrochloride. The mean exposure duration was 20 weeks (total exposure 393 patient-years). Patients were to receive 3.8 grams of colesevelam hydrochloride per day. The mean age of patients was 55.7 years, 52.8 percent of the population was male and 61.9% were Caucasian, 4.8% were Asian, and 15.9% were Black or African American. At baseline the population had a mean hemoglobin A1c (HbA1c) of 8.2%, and 26% had past medical history suggestive of microvascular complications of diabetes.

Table 3 shows adverse reactions associated with the use of colesevelam hydrochloride in patients with type 2 diabetes. These adverse reactions were not present at baseline, occurred more commonly on colesevelam hydrochloride than on placebo, and occurred in at least 2% of patients treated with colesevelam hydrochloride.

Table 3 Clinical Studies of Colesevelam Hydrochloride for Type 2 Diabetes: Adverse Reactions Reported in ≥2% of Patients and More Commonly than in Placebo
 | Colesevelam Hydrochloride N=1022 | Placebo N=1010
Constipation | 6.5% | 2.2%
Hypoglycemia | 3.4% | 3.1%
Dyspepsia | 2.8% | 1.0%
Nausea | 2.6% | 1.6%
Hypertension | 2.6% | 1.9%
Back Pain | 2.3% | 1.3%

A total of 5.3% of colesevelam hydrochloride-treated patients and 3.6% of placebo-treated patients were discontinued from the diabetes trials due to adverse reactions. This difference was driven mostly by gastrointestinal adverse reactions such as abdominal pain and constipation.

One patient in the add-on to sulfonylurea trial discontinued due to body rash and mouth blistering that occurred on the first day of dosing of colesevelam hydrochloride, which may represent a hypersensitivity reaction to colesevelam hydrochloride.

Hypertriglyceridemia

Patients with fasting serum TG levels above 500 mg/dL were excluded from the diabetes clinical trials. In the diabetes trials, 1292 (67.7%) patients had baseline fasting serum TG levels less than 200 mg/dL, 426 (22.3%) had baseline fasting serum TG levels between 200 and less than 300 mg/dL, 175 (9.2%) had baseline fasting serum TG levels between 300 and 500 mg/dL, and 16 (0.8%) had fasting serum TG levels greater than or equal to 500 mg/dL. The median baseline fasting TG concentration for the study population was 160 mg/dL; the median post-treatment fasting TG was 180 mg/dL in the colesevelam hydrochloride group and 162 mg/dL in the placebo group. Colesevelam hydrochloride therapy resulted in a median placebo-corrected increase in serum TG of 9.7% (p=0.03) in the monotherapy study and of 5% (p=0.22), 11% (p<0.001), 18% (p<0.001), and 22% (p<0.001), when added to metformin, pioglitazone, sulfonylureas, and insulin, respectively. In comparison, colesevelam hydrochloride resulted in a median increase in serum TG of 5% compared to placebo (p=0.42) in a 24-week monotherapy lipid-lowering trial.

Fasting TG concentrations ≥500 mg/dL occurred in 0.9% of colesevelam hydrochloride-treated patients compared to 0.7% of placebo-treated patients in the diabetes trials. Among these patients, the TG concentrations with colesevelam hydrochloride (median 606 mg/dL; interquartile range 570-794 mg/dL) were similar to that observed with placebo (median 663 mg/dL; interquartile range 542-984 mg/dL). Five (0.6%) patients on colesevelam hydrochloride and 3 (0.3%) patients on placebo developed TG elevations ≥1000 mg/dL.

Cardiovascular Adverse Reactions

During the diabetes trials, the incidence of patients with serious adverse reactions involving the cardiovascular system was 2.2% (22/1022) in the colesevelam hydrochloride group and 1% (10/1010) in the placebo group. These overall rates included disparate events (e.g., myocardial infarction, aortic stenosis, and bradycardia); therefore, the significance of this imbalance is unknown.

6.2 Post-marketing Experience

The following additional adverse reactions have been identified during post-approval use of colesevelam hydrochloride. Because these reactions are reported voluntarily from a population of uncertain size, it is generally not possible to reliably estimate their frequency or establish a causal relationship to drug exposure.

Adverse Reactions Resulting from Drug Interactions [see Drug Interactions (7)]: Increased seizure activity or decreased phenytoin levels in patients receiving phenytoin, reduced International Normalized Ratio (INR) in patients receiving warfarin therapy, and elevated thyroid-stimulating hormone (TSH) in patients receiving thyroid hormone replacement therapy

Gastrointestinal: Bowel obstruction (in patients with a history of bowel obstruction or resection), dysphagia or esophageal obstruction (occasionally requiring medical intervention), fecal impaction, pancreatitis, abdominal distension, exacerbation of hemorrhoids, and increased transaminases

Laboratory Abnormalities:Hypertriglyceridemia

7 DRUG INTERACTIONS

7.1 Colesevelam Hydrochloride Drug Interactions that Decrease the Exposure of the Concomitant Medication

Table 4 includes a list of drugs that decrease exposure of the concomitant medication when administered concomitantly with colesevelam hydrochloride and instructions for preventing or managing them.

Table 4 Colesevelam Hydrochloride Drug Interactions that Decrease the Exposure of the Concomitant Medication
Drugs with a Narrow Therapeutic Index
Clinical Impact: | Concomitant use with colesevelam hydrochloride may decrease the exposure of the narrow therapeutic index drug. In vivodrug interactions studies showed a decrease in exposure of cyclosporine when coadministered with colesevelam hydrochloride [see Clinical Pharmacology (12.3)].
Intervention: | Administer the narrow therapeutic index drug at least 4 hours prior to colesevelam hydrochloride. Monitor drug levels when appropriate.
Examples: | Cyclosporine
Phenytoin
Clinical Impact: | There have been postmarketing reports of increased seizure activity or decreased phenytoin levels in patients receiving phenytoin [see Adverse Reactions (6.2)].
Intervention: | Administer phenytoin 4 hours prior to colesevelam hydrochloride.
Thyroid Hormone Replacement Therapy
Clinical Impact: | In vivodrug interactions studies showed a decrease in exposure of levothyroxine when coadministered with colesevelam hydrochloride [see Clinical Pharmacology (12.3)]. There have been postmarketing reports of elevated thyroid-stimulating hormone (TSH) in patients receiving thyroid hormone replacement therapy [see Adverse Reactions (6.2)].
Intervention: | Administer thyroid hormone replacement therapy 4 hours prior to colesevelam hydrochloride.
Warfarin
Clinical Impact: | There have been postmarketing reports of reduced INR in patients receiving warfarin therapy [see Adverse Reactions (6.2)].
Intervention: | Monitor INR frequently during colesevelam hydrochloride initiation then periodically thereafter.
Oral Contraceptives Containing Ethinyl Estradiol and Norethindrone
Clinical Impact: | In vivodrug interactions studies showed a decrease in exposure of ethinyl estradiol and norethindrone when coadministered with colesevelam hydrochloride [see Clinical Pharmacology (12.3)].
Intervention: | Administer oral contraceptives containing ethinyl estradiol and norethindrone 4 hours prior to colesevelam hydrochloride.
Olmesartan Medoxomil
Clinical Impact: | In vivodrug interactions studies showed a decrease in olmesartan medoxomil when coadministered with colesevelam hydrochloride [see Clinical Pharmacology (12.3)].
Intervention: | Administer olmesartan medoxomil 4 hours prior to colesevelam hydrochloride.
Sulfonylureas
Clinical Impact: | In vivodrug interactions studies showed a decrease in sulfonylureas when coadministered with colesevelam hydrochloride [see Clinical Pharmacology (12.3)].
Intervention: | Administer sulfonylureas 4 hours prior to colesevelam hydrochloride.
Examples: | Glimepiride, glipizide, and glyburide
Oral Vitamin Supplements
Clinical Impact: | Colesevelam hydrochloride may decrease the absorption of fat-soluble vitamins A, D, E, and K [see Warnings and Precautions (5.3)].
Intervention: | Patients on oral vitamin supplementation should take their vitamins at least 4 hours prior to colesevelam hydrochloride.

7.2 Colesevelam Hydrochloride Drug Interactions that Increase the Exposure of the Concomitant Medication

Table 5 Colesevelam Hydrochloride Drug Interactions that Increase the Exposure of the Concomitant Medication
Metformin Extended Release (ER)
Clinical Impact: | In vivodrug interactions studies showed an increase in metformin extended release (ER) when coadministered with colesevelam hydrochloride [see Clinical Pharmacology (12.3)].
Intervention: | Monitor patients' glycemic control.

8 USE IN SPECIFIC POPULATIONS

8.1 Pregnancy

Risk Summary

Colesevelam hydrochloride is not absorbed systemically following oral administration, and maternal use is not expected to result in fetal exposure to the drug. Limited available data on the use of colesevelam hydrochloride are insufficient to determine a drug-associated risk of major congenital malformations or miscarriage. In animal reproduction studies, no evidence of either maternal or fetal toxicity was found in rats or rabbits exposed to colesevelam hydrochloride during the period of fetal organogenesis at 8 and 5 times, respectively, the maximum recommended human dose (MRHD) of 3.75 g/day, based on body surface area (mg/m^2). No adverse effects on offspring survival and development were observed in rats administered 5 times the MRHD (see Data). Colesevelam hydrochloride may decrease the absorption of fat-soluble vitamins [see Warnings and Precautions (5.3)]. There are no data available on the effect of colesevelam hydrochloride on the absorption of fat-soluble vitamins in pregnant women. If the patient becomes pregnant while taking colesevelam hydrochloride, the patient should be advised of the lack of known clinical benefit with continued use during pregnancy.

The estimated background risk of major birth defects and miscarriage for the indicated population is unknown. In the US general population, the estimated background risk of major birth defects and miscarriage in clinically recognized pregnancies is 2% to 4% and 15% to 20%, respectively.

Data

Human Data

There are no adequate and well-controlled studies of colesevelam hydrochloride use in pregnant women. In the postmarketing setting there have been infrequent reports of pregnancy with use of colesevelam hydrochloride and a causal association with congenital anomalies has not been established.

Animal Data

In pregnant rats given dietary doses of 0.3, 1.0, 3.0 g/kg/day colesevelam hydrochloride from gestation days 7 through 17, no teratogenic effects were observed. Exposures at 3.0 g/kg/day were 8 times the human exposure at 3.75 g/day MRHD, based on body surface area (mg/m^2).

In pregnant rabbits given oral gavage doses of 0.1, 0.5, 1.0 g/kg/day colesevelam hydrochloride from gestation days 6 through 18, no teratogenic effects were observed. Exposures at 1.0 g/kg/day were 5 times the human exposure at 3.75 g/day MRHD, based on body surface area (mg/m^2).

In pregnant rats given oral gavage doses of 0.1, 0.3, 1.0 g/kg/day colesevelam hydrochloride from gestation day 6 through lactation day 21 (weaning), no adverse effects on survival and development were observed. Exposures at 1.0 g/kg/day were 5 times the human exposure at 3.75 g/day MRHD, based on body surface area (mg/m^2).

8.2 Lactation

Risk Summary

Colesevelam hydrochloride is not absorbed systemically by the mother following oral administration, and breastfeeding is not expected to result in exposure of the child to colesevelam hydrochloride.

8.3 Females and Males of Reproductive Potential

Contraception

Use of colesevelam hydrochloride may reduce the efficacy of oral contraceptives. Advise patients to take oral contraceptives at least 4 hours prior to taking colesevelam hydrochloride [see Drug Interactions (7)].

8.4 Pediatric Use

Primary Hyperlipidemia

The safety and effectiveness of colesevelam hydrochloride to reduce LDL-C levels in boys and postmenarchal girls 10 to 17 years of age with HeFH who are unable to reach LDL-C target levels despite an adequate trial of dietary therapy and lifestyle modification have been established. Use of colesevelam hydrochloride for this indication is supported by a study in 129 colesevelam hydrochloride-treated pediatric patients aged 10 to 17 years with HeFH [see Clinical Studies (14.1)] . Adverse reactions commonly observed in pediatric patients compared to placebo, but not in adults, included headache (3.9%), creatine phosphokinase increase (2.3%), and vomiting (2.3%) [see Adverse Reactions (6.1)] . There were no significant effects on fat-soluble vitamin levels or clotting factors in the adolescent boys or girls relative to placebo.Due to colesevelam hydrochloride tablet size, colesevelam hydrochloride for oral suspension is recommended for use in the pediatric population [see Dosage and Administration (2.2, 2.4)] . The safety and effectiveness of colesevelam hydrochloride in pediatric patients with HeFH less than 10 years of age or in premenarchal females have not been established.

Type 2 Diabetes Mellitus

The safety and effectiveness of colesevelam hydrochloride to improve glycemic control in pediatric patients with type 2 diabetes mellitus have not been established. Effectiveness was not demonstrated in a 6-month, adequate and well-controlled study conducted in 141 colesevelam hydrochloride-treated pediatric patients aged 10 to 17 years with type 2 diabetes mellitus.

8.5 Geriatric Use

Primary Hyperlipidemia

Of the 1350 patients enrolled in the hyperlipidemia clinical studies, 349 (26%) were ≥65 years old, and 58 (4%) were ≥75 years old. No overall differences in safety or effectiveness were observed between these subjects and younger subjects, and other reported clinical experience has not identified differences in responses between the elderly and younger patients, but greater sensitivity of some older individuals cannot be ruled out.

Type 2 Diabetes Mellitus

Of the 2048 patients enrolled in the six diabetes studies, 397 (19%) were ≥65 years old, and 36 (2%) were ≥75 years old. In these trials, colesevelam hydrochloride 3.8 g/day or placebo was added onto background anti-diabetic therapy. No overall differences in safety or effectiveness were observed between the elderly and younger patients, but greater sensitivity of some older individuals cannot be ruled out.

8.6 Renal Impairment

Type 2 Diabetes Mellitus

Of the 2048 patients enrolled in the six diabetes studies, 807 (39%) had mild renal insufficiency (creatinine clearance [CrCl] 50-<80 mL/min), 61 (3%) had moderate renal insufficiency (CrCl 30-<50 mL/min), and none had severe renal insufficiency (CrCl <30 mL/min), as estimated from baseline serum creatinine using the Modification of Diet in Renal Disease (MDRD) equation. No overall differences in safety or effectiveness were observed between patients with CrCl <50 mL/min (n=53) and those with a CrCl ≥50 mL/min (n=1075) in the add-on to metformin, sulfonylureas, and insulin diabetes studies. In the monotherapy study and add-on to pioglitazone study, only 3 and 5 patients, respectively, had moderate renal insufficiency.

10 OVERDOSAGE

Colesevelam hydrochloride is not absorbed and the risk of systemic toxicity is low. Excessive doses of colesevelam hydrochloride may cause more severe local gastrointestinal effects (e.g., constipation).

11 DESCRIPTION

Colesevelam hydrochloride is a non-absorbed, polymeric, lipid-lowering and glucose-lowering agent for oral administration. Colesevelam hydrochloride is a high-capacity bile acid-binding molecule.

Colesevelam hydrochloride is poly(allylamine hydrochloride) cross-linked with epichlorohydrin and alkylated with 1-bromodecane and (6-bromohexyl)-trimethylammonium bromide. The chemical name (IUPAC) of colesevelam hydrochloride is allylamine polymer with 1-chloro-2,3-epoxypropane,[6-(allylamino)-hexyl] trimethylammonium chloride and N-allyldecylamine, hydrochloride. The chemical structure of colesevelam hydrochloride is represented by the following formula:

wherein (a) represents allyl amine monomer units that have not been alkylated by either of the 1-bromodecane or (6-bromohexyl)-trimethylammonium bromide alkylating agents or cross-linked by epichlorohydrin; (b) represents allyl amine units that have undergone cross-linking with epichlorohydrin; (c) represents allyl amine units that have been alkylated with a decyl group; (d) represents allyl amine units that have been alkylated with a (6-trimethylammonium) hexyl group, and m represents a number ≥100 to indicate an extended polymer network. A small amount of the amines are dialkylated and are not depicted in the formula above. No regular order of the groups is implied by the structure; cross-linking and alkylation are expected to occur randomly along the polymer chains. A large amount of the amines are protonated. The polymer is depicted in the hydrochloride form; a small amount of the halides are bromide. Colesevelam hydrochloride is hydrophilic and insoluble in water.

Colesevelam hydrochloride tablets are off-white, oval, film-coated, solid tablets each containing 625 mg colesevelam hydrochloride. In addition, each tablet contains the following inactive ingredients: magnesium stearate, microcrystalline cellulose, silicon dioxide, HPMC (hydroxypropyl methylcellulose), and acetylated monoglyceride. The tablets are imprinted using a water-soluble black ink (<5 calories per 6 tablets).

Colesevelam hydrochloride for oral suspension is a citrus-flavored, white to pale yellow powder containing yellow granules packaged in a packet containing 3.75 gram colesevelam hydrochloride. In addition, each packet contains the following inactive ingredients: lemon flavor, orange flavor, propylene glycol alginate, simethicone, aspartame, citric acid, medium chain triglycerides, and magnesium trisilicate (<5 calories per 3.75 gram single-dose packet). PHENYLKETONURICS: Colesevelam hydrochloride for oral suspension contains 27 mg phenylalanine per 3.75 gram dose.

12 CLINICAL PHARMACOLOGY

12.1 Mechanism of Action

Primary Hyperlipidemia: Colesevelam hydrochloride, the active pharmaceutical ingredient, is a non-absorbed, lipid-lowering polymer that binds bile acids in the intestine, impeding their reabsorption. As the bile acid pool becomes depleted, the hepatic enzyme, cholesterol 7-α-hydroxylase, is upregulated, which increases the conversion of cholesterol to bile acids. This causes an increased demand for cholesterol in the liver cells, resulting in the dual effect of increasing transcription and activity of the cholesterol biosynthetic enzyme, HMG-CoA reductase, and increasing the number of hepatic LDL receptors. These compensatory effects result in increased clearance of LDL-C from the blood, resulting in decreased serum LDL-C levels. Serum TG levels may increase or remain unchanged.

Type 2 Diabetes Mellitus: The mechanism by which colesevelam hydrochloride improves glycemic control is unknown.

12.2 Pharmacodynamics

A maximum therapeutic response to the lipid-lowering effects of colesevelam hydrochloride was achieved within 2 weeks and was maintained during long-term therapy. In the diabetes clinical studies, a therapeutic response to colesevelam hydrochloride, as reflected by a reduction in HbA1c, was initially noted following 4-6 weeks of treatment and reached maximal or near-maximal effect after 12-18 weeks of treatment.

12.3 Pharmacokinetics

Absorption

Colesevelam hydrochloride is a hydrophilic, water-insoluble polymer that is not hydrolyzed by digestive enzymes and is not absorbed.

Distribution

Colesevelam hydrochloride is not absorbed, and therefore, its distribution is limited to the gastrointestinal tract.

Elimination

Metabolism

Colesevelam hydrochloride is not metabolized systemically and does not interfere with systemic drug-metabolizing enzymes such as cytochrome P450.

Excretion

In 16 healthy volunteers, an average of 0.05% of administered radioactivity from a single^14C-labeled colesevelam hydrochloride dose was excreted in the urine.

Drug Interaction Studies

Drug interactions between colesevelam and concomitantly administered drugs were screened through in vitrostudies and confirmed in in vivostudies. In vitrostudies demonstrated that cephalexin, metformin, and ciprofloxacin had negligible binding to colesevelam hydrochloride. Therefore, an in vivopharmacokinetic interaction of colesevelam hydrochloride with these drugs is unlikely. Colesevelam hydrochloride was found to have no significant effect on the bioavailability of aspirin, atenolol, digoxin, enalapril, fenofibrate, lovastatin, metoprolol, phenytoin, pioglitazone, quinidine, rosiglitazone, sitagliptin, valproic acid, and warfarin. The results of additional in vivodrug interactions of colesevelam hydrochloride are presented in Table 6.

Table 6 Mean Change in Drug Exposure (AUC0-∞and Cmax) when Administered with Colesevelam Hydrochloride (3.75 g) [With verapamil, the dose of colesevelam hydrochloride was 4.5 g.]
Drug | Dose | Co-administered |  | 1 hr prior to Colesevelam Hydrochloride |  | 4 hrs prior to Colesevelam Hydrochloride
 |  | AUC0-∞ | Cmax | AUC0-∞ | Cmax | AUC0-∞ | Cmax
Cyclosporine | 200 mg | -34% | -44% | N/A | N/A | N/A | N/A
Ethinyl Estradiol [Oral contraceptive containing norethindrone and ethinyl estradiol] | 0.035 mg | -24% | -24% | -18% | -1% | -12% | 0%
Glimepiride | 4 mg | -18% | -8% | N/A | N/A | -6% | 3%
Glipizide | 20 mg | -12% | -13% | N/A | N/A | -4% | 0%
Glyburide | 3 mg | -32% | -47% | -20% | -15% | -7% | 4%
Levothyroxine | 600 µg | -22% | -33% | 6% | -2% | 1% | 8%
Metformin ER | 1500 mg | 44% | 8% | N/A | N/A | N/A | N/A
Norethindrone | 1 mg | -1% | -20% | 5% | -3% | 6% | 7%
Olmesartan Medoxomil | 40 mg | -39% | -28% | N/A | N/A | -15% | -4%
Repaglinide | 2 mg | -7% | -19% | -6% | -1% | N/A | N/A
Verapamil Sustained Release | 240 mg | -31% | -11% | N/A | N/A | N/A | N/A
N/A − not available

13 NONCLINICAL TOXICOLOGY

13.1 Carcinogenesis, Mutagenesis, Impairment of Fertility

Carcinogenesis

A 104-week carcinogenicity study with colesevelam hydrochloride was conducted in CD-1 mice, at oral dietary doses up to 3 g/kg/day. This dose was approximately 50 times the maximum recommended human dose of 4.5 g/day, based on body weight, mg/kg. There were no significant drug-induced tumor findings in male or female mice. In a 104-week carcinogenicity study with colesevelam hydrochloride in Harlan Sprague-Dawley rats, a statistically significant increase in the incidence of pancreatic acinar cell adenoma was seen in male rats at doses >1.2 g/kg/day (approximately 20 times the maximum human dose, based on body weight, mg/kg) (trend test only). A statistically significant increase in thyroid C-cell adenoma was seen in female rats at 2.4 g/kg/day (approximately 40 times the maximum human dose, based on body weight, mg/kg).

Mutagenesis

Colesevelam hydrochloride and 4 degradants present in the drug substance have been evaluated for mutagenicity in the Ames test and a mammalian chromosomal aberration test. The 4 degradants and an extract of the parent compound did not exhibit genetic toxicity in an in vitrobacterial mutagenesis assay in S. typhimuriumand E. coli(Ames assay) with or without rat liver metabolic activation. An extract of the parent compound was positive in the Chinese Hamster Ovary (CHO) cell chromosomal aberration assay in the presence of metabolic activation and negative in the absence of metabolic activation. The results of the CHO cell chromosomal aberration assay with 2 of the 4 degradants, decylamine HCl and aminohexyltrimethyl ammonium chloride HCl, were equivocal in the absence of metabolic activation and negative in the presence of metabolic activation. The other 2 degradants, didecylamine HCl and 6-decylamino-hexyltrimethyl ammonium chloride HCl, were negative in the presence and absence of metabolic activation.

Impairment of Fertility

Colesevelam hydrochloride did not impair fertility in rats at doses up to 3 g/kg/day (approximately 50 times the maximum human dose, based on body weight, mg/kg).

13.2 Animal Toxicology and/or Pharmacology

Reproductive Toxicology Studies

Reproduction studies have been performed in rats and rabbits at doses up to 3 g/kg/day and 1 g/kg/day, respectively (approximately 50 and 17 times the maximum human dose, based on body weight, mg/kg) and have revealed no evidence of harm to the fetus due to colesevelam hydrochloride.

14 CLINICAL STUDIES

14.1 Primary Hyperlipidemia

Colesevelam hydrochloride reduces total cholesterol (TC), LDL-C, apolipoprotein B (Apo B), and non-high-density lipoprotein cholesterol (non-HDL-C) when administered alone or in combination with a statin in patients with primary hyperlipidemia.

Approximately 1600 patients were studied in 9 clinical trials with treatment durations ranging from 4 to 50 weeks. With the exception of one open-label, uncontrolled, long-term extension study, all studies were multicenter, randomized, double-blind, and placebo-controlled. A maximum therapeutic response to colesevelam hydrochloride was achieved within 2 weeks and was maintained during long-term therapy.

Monotherapy

In a study in patients with LDL-C between 130 mg/dL and 220 mg/dL (mean 158 mg/dL), colesevelam hydrochloride was given for 24 weeks in divided doses with the morning and evening meals.

As shown in Table 7, the mean LDL-C reductions were 15% and 18% at the 3.8 g and 4.5 g doses. The respective mean TC reductions were 7% and 10%. The mean Apo B reductions were 12% in both treatment groups. Colesevelam hydrochloride at both doses increased HDL-C by 3%. Increases in TG of 9-10% were observed at both colesevelam hydrochloride doses, but the changes were not statistically different from placebo.

Table 7 Response to Colesevelam Hydrochloride Monotherapy in a 24-Week Trial - Percent Change in Lipid Parameters from Baseline
Grams/Day | N | TC | LDL-C | Apo B | HDL-C [Median % change from baseline] | Non-HDL-C | TG
Placebo | 88 | +1 | 0 | 0 | −1 | +1 | +5
3.8 g (6 tablets) | 95 | −7 [p<0.05 for lipid parameters compared to placebo, for Apo B compared to baseline] | −15 | −12 | +3 | −10 | +10
4.5 g (7 tablets) | 94 | −10 | −18 | −12 | +3 | −13 | +9

In a study in 98 patients with LDL-C between 145 mg/dL and 250 mg/dL (mean 169 mg/dL), colesevelam hydrochloride 3.8 g was given for 6 weeks as a single dose with breakfast, as a single dose with dinner, or as divided doses with breakfast and dinner. The mean LDL-C reductions were 18%, 15%, and 18% for the 3 dosing regimens, respectively. The reductions with these 3 regimens were not statistically different from one another.

Combination Therapy

Co-administration of colesevelam hydrochloride and a statin (atorvastatin, lovastatin, or simvastatin) in 3 clinical studies demonstrated an additive reduction of LDL-C. The mean baseline LDL-C was 184 mg/dL in the atorvastatin study (range 156-236 mg/dL), 171 mg/dL in the lovastatin study (range 115-247 mg/dL), and 188 mg/dL in the simvastatin study (range 148-352 mg/dL). As demonstrated in Table 8, colesevelam hydrochloride doses of 2.3 g to 3.8 g resulted in an additional 8% to 16% reduction in LDL-C above that seen with the statin alone.

Table 8 Response to Colesevelam Hydrochloride in Combination with Atorvastatin, Simvastatin, or Lovastatin - Percent Change in Lipid Parameters
Dose/Day | N | TC | LDL-C | Apo B | HDL-C [Median % change from baseline] | Non-HDL-C | TG
Atorvastatin Trial (4-week)
Placebo | 19 | +4 | +3 | −3 | +4 | +4 | +10
Atorvastatin 10 mg | 18 | −27 [p<0.05 for lipid parameters compared to placebo, for Apo B compared to baseline] | −38 | −32 | +8 | −35 | −24
Colesevelam hydrochloride 3.8 g/Atorvastatin 10 mg | 18 | −31 | −48 | −38 | +11 | −40 | −1
Atorvastatin 80 mg | 20 | −39 | −53 | −46 | +6 | −50 | −33
Simvastatin Trial (6-week)
Placebo | 33 | −2 | −4 | −4 | −3 | −2 | +6
Simvastatin 10 mg | 35 | −19 | −26 | −20 | +3 | −24 | −17
Colesevelam hydrochloride 3.8 g/Simvastatin 10 mg | 34 | −28 | −42 | −33 | +10 | −37 | −12
Simvastatin 20 mg | 39 | −23 | −34 | −26 | +7 | −30 | −12
Colesevelam hydrochloride 2.3 g/Simvastatin 20 mg | 37 | −29 | −42 | −32 | +4 | −37 | −12
Lovastatin Trial (4-week)
Placebo | 26 | +1 | 0 | 0 | +1 | +1 | +1
Lovastatin 10 mg | 26 | −14 | −22 | −16 | +5 | −19 | 0
Colesevelam hydrochloride 2.3 g/Lovastatin 10 mg Together | 27 | −21 | −34 | −24 | +4 | −27 | −1
Colesevelam hydrochloride 2.3 g/Lovastatin 10 mg Apart | 23 | −21 | −32 | −24 | +2 | −28 | −2

In all 3 studies, the LDL-C reduction achieved with the combination of colesevelam hydrochloride and any given dose of statin therapy was statistically superior to that achieved with colesevelam hydrochloride or that dose of the statin alone. The LDL-C reduction with atorvastatin 80 mg was not statistically significantly different from the combination of colesevelam hydrochloride 3.8 g and atorvastatin 10 mg.

Pediatric Therapy

The safety and efficacy of colesevelam hydrochloride in pediatric patients were evaluated in an 8-week, multicenter, randomized, double-blind, placebo-controlled, parallel-group study followed by an open-label phase, in 194 boys and postmenarchal girls 10-17 years of age (mean age 14.1 years) with HeFH, taking a stable dose of an FDA-approved statin (with LDL-C >130 mg/dL) or naïve to lipid-lowering therapy (with LDL-C >160 mg/dL). This study had 3 periods: a single-blind, placebo stabilization period; an 8-week, randomized, double-blind, parallel-group, placebo-controlled treatment period; and an 18-week, open-label treatment period. Forty-seven (24%) patients were taking statins and 147 (76%) patients were statin-naïve at screening. The mean baseline LDL-C at Day 1 was approximately 199 mg/dL.

During the double-blind treatment period, patients were assigned randomly to treatment: Colesevelam hydrochloride 3.8 g/day (n=64), Colesevelam hydrochloride 1.9 g/day (n=65), or placebo (n=65). In total, 186 patients completed the double-blind treatment period. After 8 weeks of treatment, Colesevelam hydrochloride 3.8 g/day significantly decreased plasma levels of LDL-C, non-HDL-C, TC, and Apo B and significantly increased HDL-C. A moderate, non-statistically significant increase in TG was observed versus placebo (Table 9).

Table 9 Response to Colesevelam Hydrochloride 3.8 g Compared to Placebo in Pediatric Patients 10-17 Years of Age − Mean Percent Change in Lipid Parameters from Baseline to Week 8
Treatment Difference | TC | LDL-C | Apo B | HDL-C | Non-HDL-C | TG [For triglycerides, median % change from baseline]
 | (N=128) | (N=128) | (N=124) | (N=128) | (N=128) | (N=128)
Colesevelam hydrochloride 3.8 g vs Placebo | -7 [p≤0.05 for lipid parameters compared to placebo] | -13 | -8 | +6 | −11 | +5
Values represent LS mean. Only patients with values at both study baseline and endpoint are included in this table. Study baseline was defined as the last value measured before or on Day 1 prior to the first dose of randomized study medication.
Results were based on the ITT population with LOCF.

During the open-label treatment period patients were treated with colesevelam hydrochloride 3.8 g/day. In total, 173 (89%) patients completed 26 weeks of treatment. Results at Week 26 were consistent with those at Week 8.

14.2 Type 2 Diabetes Mellitus

Colesevelam hydrochloride has been studied as monotherapy and in combination with metformin, pioglitazone, sulfonylureas, and insulin. In these studies, colesevelam hydrochloride and placebo were administered either as 3 tablets twice daily with lunch and dinner or as 6 tablets with dinner alone.

Monotherapy

The efficacy of colesevelam hydrochloride 3.8 g/day as anti-diabetes monotherapy was evaluated in a randomized double-blind, placebo-controlled trial involving 357 patients (176 colesevelam hydrochloride and 181 placebo) with type 2 diabetes mellitus who were treatment-naïve or had not received antihyperglycemic medication within 3 months prior to the start of the study. Statin use at baseline was reported in 13% of the colesevelam hydrochloride-treated patients and 16% of the placebo-treated patients.

Colesevelam hydrochloride resulted in a statistically significant reduction in HbA1c of 0.27% compared to placebo (Table 10).

The mean baseline LDL-C was 121 mg/dL in the monotherapy trial. Colesevelam hydrochloride treatment resulted in a placebo-corrected 11% reduction in LDL-C. Colesevelam hydrochloride treatment also reduced serum TC, ApoB, and non-HDL-C (Table 11). The mean change in body weight was -0.6 kg for colesevelam hydrochloride and -0.7 kg for placebo treatment groups.

Table 10 Glycemic Parameters in a 24-Week Placebo-Controlled Study of Colesevelam Hydrochloride Monotherapy in Patients with Type 2 Diabetes
 | Colesevelam Hydrochloride 3.8 g/day | Placebo
HbA1c (%), Mean
N | 175 | 169
Baseline | 8.25 | 8.17
Change from baseline [Least-squares mean change calculated from an Analysis of Covariance model] | -0.26 | 0.01
Treatment difference (p-value) | -0.27 (p=0.013)
FPG (mg/dL), Mean
N | 172 | 166
Baseline | 172 | 168
Change from baseline | -4.6 | 5.7
Treatment difference (p-value) | -10.3 (p=0.037 [Nominal p=value, not controlled for multiplicity testing])
FPG = fasting plasma glucose

Table 11 Percent Change in Lipid Parameters in a 24-Week Placebo-Controlled Study of Colesevelam Hydrochloride Monotherapy in Patients with Type 2 Diabetes
Dose/Day | N [The number of patients with analyzable data, i.e., a baseline and post-treatment value (last observation carried forward), varied slightly among different parameters. The N given represents the smallest number of patients included in the analysis for any parameter.] | TC | LDL-C | Apo B | HDL-C | Non-HDL-C | TG [Median % change from baseline]
Colesevelam hydrochloride 3.8 g | 162 | -3.3 [p<0.001 for lipid parameters compared to placebo (This more stringent criterion for statistical significance accounts for multiplicity testing of the lipid parameters, which were secondary endpoints in the diabetes trials.)] | -10.0 | -5.6 | 1.7 | -4.4 | 15.5
Placebo | 160 | 1.8 | 1.2 | 0.9 | -0.1 | 3.0 | 5.8

Add-on Combination Therapy

The efficacy of colesevelam hydrochloride 3.8 g/day in patients with type 2 diabetes mellitus was evaluated in 5 double-blind, placebo-controlled add-on therapy trials involving a total of 1691 patients with baseline HbA1c 7.5-9.5%. Patients were enrolled and maintained on their pre-existing, stable, background anti-diabetic regimen. Statin use at baseline was reported in 41% of the colesevelam hydrochloride-treated patients and 48% of the placebo-treated patients.

In 3 add-on combination therapy trials (metformin, sulfonylurea and insulin), treatment with colesevelam hydrochloride resulted in a statistically significant reduction in HbA1c of 0.5% compared to placebo. Similar placebo-corrected reductions in HbA1c occurred in patients who received colesevelam hydrochloride in combination with metformin, sulfonylurea, or insulin monotherapy or combinations of these therapies with other anti-diabetic agents. In the pioglitazone trial, treatment with colesevelam hydrochloride resulted in a statistically significant reduction in HbA1c of 0.32% compared to placebo. In the metformin, pioglitazone, and sulfonylurea trials, treatment with colesevelam hydrochloride also resulted in statistically significant reductions in FPG of at least 14 mg/dL compared to placebo.

Colesevelam hydrochloride had consistent effects on HbA1c across subgroups of age, gender, race, body mass index, and baseline HbA1c. Colesevelam hydrochloride's effects on HbA1c were also similar for the two dosing regimens (3 tablets with lunch and with dinner or 6 tablets with dinner alone).

The mean baseline LDL-C was 104 mg/dL in the metformin study (range 32-214 mg/dL), 107 mg/dL in the pioglitazone study (range 48-263 mg/dL), 106 mg/dL in the sulfonylurea study (range 41-264 mg/dL), 102 mg/dL in the insulin study (range 35-204 mg/dL). In these trials, colesevelam hydrochloride treatment was associated with a 12% to 16% reduction in LDL-C levels. The percentage decreases in LDL-C were of similar magnitude to those observed in patients with primary hyperlipidemia. Colesevelam hydrochloride treatment was associated with statistically significant increases in TG levels in the studies of patients on insulin, patients on a sulfonylurea, and patients on pioglitazone but not in the study of patients on metformin. The clinical significance of these increases is unknown. Colesevelam hydrochloride is contraindicated in patients with TG levels >500 mg/dL [see Contraindications (4)] , and periodic monitoring of lipid parameters including TG is recommended [see Warnings and Precautions (5.1)and Adverse Reactions (6.1)] .

Body weight did not significantly increase from baseline with colesevelam hydrochloride therapy, compared with placebo, in any of the add-on combination diabetes studies.

Add-on Combination Therapy with Metformin

Colesevelam hydrochloride 3.8 g/day or placebo was added to background anti-diabetic therapy in a 26-week trial of 316 patients already receiving treatment with metformin alone (N=159) or metformin in combination with other oral agents (N=157). A total of 60% of these patients were receiving ≥1,500 mg/day of metformin. In combination with metformin, colesevelam hydrochloride resulted in statistically significant placebo-corrected reductions in HbA1c and FPG (Table 12). Colesevelam hydrochloride also reduced TC, LDL-C, Apo B, and non-HDL-C (Table 13). The mean percent change in serum LDL-C levels with colesevelam hydrochloride compared to placebo was -16% among statin users and statin non-users; the median percent change in serum TG levels with colesevelam hydrochloride compared to placebo was -2% among statin users and 10% among statin non-users. The mean change in body weight was -0.5 kg for colesevelam hydrochloride and -0.3 kg for placebo.

Table 12 Glycemic Parameters in a 26-Week Placebo-Controlled Study of Colesevelam Hydrochloride in Combination with Metformin in Patients with Type 2 Diabetes
 | Total Patient Population |  | Metformin Alone |  | Metformin in Combination with Other Oral Anti-diabetic Agents
 | Colesevelam Hydrochloride 3.8 g/day | Placebo | Colesevelam Hydrochloride 3.8 g/day | Placebo | Colesevelam Hydrochloride 3.8 g/day | Placebo
HbA1c (%), Mean
N | 148 | 152 | 79 | 76 | 69 | 76
Baseline | 8.1 | 8.1 | 8.2 | 8.2 | 8.1 | 8.0
Change from baseline [Least-squares mean change calculated from an Analysis of Covariance model] | -0.4 | 0.2 | -0.4 | 0.0 | -0.4 | 0.3
Treatment difference (p-value) | -0.5 (p<0.001) |  | -0.5 (p=0.002) |  | -0.6 (p<0.001)
FPG (mg/dL), Mean
N | 149 | 152 | 79 | 76 | 70 | 76
Baseline | 178 | 174 | 184 | 180 | 171 | 168
Change from baseline | -3 | 11 | -7 | 8 | 0 | 13
Treatment difference (p-value) | -14 (p=0.01) |  | -14 (p=0.07) |  | -14 (p=0.10)

Table 13 Percent Change in Lipid Parameters in a 26-Week Placebo-Controlled Study of Colesevelam Hydrochloride in Combination with Metformin in Patients with Type 2 Diabetes
Dose/Day | N [The number of patients with analyzable data, i.e., a baseline and post-treatment value (last observation carried forward), varied slightly among different parameters. The N given represents the smallest number of patients included in the analysis for any parameter.] | TC | LDL-C | Apo B | HDL-C | Non-HDL-C | TG [Median % change from baseline]
Total Patient Population
Colesevelam hydrochloride 3.8 g | 125 | -4 [p<0.001 for lipid parameters compared to placebo (This more stringent criterion for statistical significance accounts for multiplicity testing of the lipid parameters, which were secondary endpoints in the diabetes trials.)] | -12 | -4 | 1 | -6 | 12
Placebo | 126 | 3 | 4 | 4 | 0 | 5 | 7
Metformin Alone
Colesevelam hydrochloride 3.8 g | 66 | -3 | -9 | -2 | 1 | -4 | 15
Placebo | 61 | 2 | 0 | 1 | -2 | 4 | 8
Metformin in Combination with Other Oral Anti-diabetic Agents
Colesevelam hydrochloride 3.8 g | 59 | -6 | -15 | -6 | 1 | -7 | 8
Placebo | 65 | 4 | 7 | 7 | 2 | 6 | 5

Add-on Combination Therapy with Pioglitazone

Colesevelam hydrochloride 3.8 g/day or placebo was added to background anti-diabetic therapy in a 24-week trial of 562 patients already receiving treatment with pioglitazone alone (N=51) or pioglitazone in combination with other oral agents (N=511). Of these, most were on dual therapy with metformin (N=298) or triple therapy with metformin and a sulfonylurea (N=139). In combination with pioglitazone-based therapy, colesevelam hydrochloride resulted in statistically significant reductions in HbA1c and FPG compared to placebo (Table 14). Colesevelam hydrochloride also reduced TC, LDL-C, Apo B, and non-HDL-C but increased serum TG (Table 15). The mean change in body weight was 0.8 kg for colesevelam hydrochloride and 0.4 kg for placebo.

Table 14 Glycemic Parameters in a 24-Week Placebo-Controlled Study of Colesevelam Hydrochloride in Combination with Pioglitazone-Based Therapy in Patients with Type 2 Diabetes
 | Colesevelam Hydrochloride 3.8 g/day | Placebo
HbA1c (%), Mean
N | 271 | 276
Baseline | 8.2 | 8.1
Change from baseline [Least-squares mean change calculated from an Analysis of Covariance model] | -0.34 | -0.02
Treatment difference (p-value) | -0.32 (0.0001)
FPG (mg/dL), Mean
N | 268 | 270
Baseline | 155 | 157
Change from baseline | -4.8 | +9.9
Treatment difference (p-value) | -14.7 (<0.0001)

Table 15 Percent Change in Lipid Parameters in a 24-Week Placebo-Controlled Study of Colesevelam Hydrochloride in Combination with Pioglitazone-Based Therapy in Patients with Type 2 Diabetes
Dose/Day | N [The N given represents the smallest number of patients included in the analysis for any parameter.] | TC | LDL-C | Apo B | HDL-C | Non-HDL-C | TG [Median % change from baseline]
Total Patient Cohort
Colesevelam hydrochloride 3.8 g | 262 | -3 [p<0.001 for lipid parameters compared to placebo] | -9 | -5 | +3 | -5 | +14
Placebo | 262 | +3 | +7 | +4 | +1 | +5 | +2

Add-on Combination Therapy with Sulfonylurea

Colesevelam hydrochloride 3.8 g/day or placebo was added to background anti-diabetic therapy in a 26-week trial of 460 patients already treated with sulfonylurea alone (N=156) or sulfonylurea in combination with other oral agents (N=304). A total of 72% of these patients were receiving at least half-maximal doses of sulfonylurea therapy. In combination with a sulfonylurea, colesevelam hydrochloride resulted in statistically significant placebo-corrected reductions in HbA1c and FPG (Table 16). Colesevelam hydrochloride also reduced TC, LDL-C, Apo B, and non-HDL-C, but increased serum TG (Table 17). The mean percent change in serum LDL-C levels with colesevelam hydrochloride compared to placebo was -18% among statin users and -15% among statin non-users; the median percent increase in serum TG with colesevelam hydrochloride compared to placebo was 29% among statin users and 9% among statin non-users. The mean change in body weight was 0.0 kg for colesevelam hydrochloride and -0.4 kg for placebo.

Table 16 Glycemic Parameters in a 26-Week Placebo-Controlled Study of Colesevelam Hydrochloride in Combination with Sulfonylurea in Patients with Type 2 Diabetes
 | Total Patient Population |  | Sulfonylurea Alone |  | Sulfonylurea in Combination with Other Oral Anti-diabetic Agents
 | Colesevelam Hydrochloride 3.8 g/day | Placebo | Colesevelam Hydrochloride 3.8 g/day | Placebo | Colesevelam Hydrochloride 3.8 g/day | Placebo
HbA1c (%), Mean
n | 218 | 218 | 69 | 80 | 149 | 138
Baseline | 8.2 | 8.3 | 8.2 | 8.4 | 8.2 | 8.3
Change from baseline [Least-squares mean change calculated from an Analysis of Covariance model] | -0.3 | 0.2 | -0.3 | 0.5 | -0.4 | 0.0
Treatment difference (p-value) | -0.5 (p<0.001) |  | -0.8 (p<0.001) |  | -0.4 (p<0.001)
FPG (mg/dL), Mean
n | 218 | 217 | 70 | 80 | 148 | 137
Baseline | 177 | 181 | 181 | 186 | 175 | 178
Change from baseline | -4 | 10 | 3 | 15 | -11 | 4
Treatment difference (p-value) | -14 (p=0.009) |  | -12 (p=0.18) |  | -14 (p=0.03)

Table 17 Percent Change in Lipid Parameters in a 26-Week Placebo-Controlled Study of Colesevelam Hydrochloride in Combination with Sulfonylurea in Patients with Type 2 Diabetes
Dose/Day | N [The number of patients with analyzable data, i.e., a baseline and post-treatment value (last observation carried forward), varied slightly among different parameters. The N given represents the smallest number of patients included in the analysis for any parameter.] | TC | LDL-C | Apo B | HDL-C | Non-HDL-C | TG [Median % change from baseline]
Total Patient Population
Colesevelam hydrochloride 3.8 g | 186 | -5 [p<0.001 for lipid parameters compared to placebo (This more stringent criterion for statistical significance accounts for multiplicity testing of the lipid parameters, which were secondary endpoints in the diabetes trials.)] | -16 | -6 | 1 | -6 | 20
Placebo | 193 | 0 | 1 | 1 | 0 | 1 | 1
Sulfonylurea Alone
Colesevelam hydrochloride 3.8 g | 57 | -5 | -14 | -5 | -1 | -6 | 17
Placebo | 68 | 0 | 1 | 1 | 1 | 0 | -1
Sulfonylurea in Combination with Other Oral Anti-diabetic Agents
Colesevelam hydrochloride 3.8 g | 129 | -5 | -18 | -7 | 1 | -6 | 21
Placebo | 125 | 0 | 0 | 1 | 0 | 1 | 2

Add-on Combination Therapy with Insulin

Colesevelam hydrochloride 3.8 g/day or placebo was added to background anti-diabetic therapy in a 16-week trial of 287 patients already treated with insulin alone (N=116) or insulin in combination with oral agents (N=171). At baseline, the median daily insulin dose was 70 units in the colesevelam hydrochloride group and 65 units in the placebo group. In combination with insulin, colesevelam hydrochloride resulted in a statistically significant placebo-corrected reduction in HbA1c (Table 18). Colesevelam hydrochloride also reduced LDL-C and Apo B, but increased serum TG (Table 19). The mean percent change in serum LDL-C levels with colesevelam hydrochloride compared to placebo was -13% among statin users and statin non-users; the median percent increase in serum TG levels with colesevelam hydrochloride compared to placebo was 24% among statin users and 17% among statin non-users. The mean change in body weight was 0.6 kg for colesevelam hydrochloride and 0.2 kg for placebo.

Table 18 Glycemic Parameters in a 16-Week Placebo-Controlled Study of Colesevelam Hydrochloride in Combination with Insulin in Patients with Type 2 Diabetes
 | Total Patient Population |  | Insulin Alone |  | Insulin in Combination with Oral Anti-diabetic Agents
 | Colesevelam Hydrochloride 3.8 g/day | Placebo | Colesevelam Hydrochloride 3.8 g/day | Placebo | Colesevelam Hydrochloride 3.8 g/day | Placebo
HbA1c (%), Mean
n | 144 | 136 | 54 | 55 | 90 | 81
Baseline | 8.3 | 8.2 | 8.2 | 8.3 | 8.3 | 8.2
Change from baseline [Least-squares mean change calculated from an Analysis of Covariance model] | -0.4 | 0.1 | -0.4 | 0.2 | -0.4 | 0.0
Treatment difference (p-value) | -0.5 (p<0.001) |  | -0.6 (p<0.001) |  | -0.4 (p<0.001)
FPG (mg/dL), Mean
n | 144 | 136 | 54 | 55 | 90 | 81
Baseline | 165 | 151 | 165 | 163 | 165 | 143
Change from baseline | 2 | 16 | 8 | 17 | -4 | 14
Treatment difference (p-value) | -15 (p=0.08) |  | -9 (p=0.51) |  | -18 (p=0.09)

Table 19 Percent Change in Lipid Parameters in a 16-Week Placebo-Controlled Study of Colesevelam Hydrochloride in Combination with Insulin in Patients with Type 2 Diabetes
Dose/Day | N [The number of patients with analyzable data, i.e., a baseline and post-treatment value (last observation carried forward), varied slightly among different parameters. The N given represents the smallest number of patients included in the analysis for any parameter.] | TC | LDL-C | Apo B | HDL-C | Non-HDL-C | TG [Median % change from baseline]
Total Patient Cohort
Colesevelam hydrochloride 3.8 g | 129 | -3 | -12 [p<0.001 for lipid parameters compared to placebo (This more stringent criterion for statistical significance accounts for multiplicity testing of the lipid parameters, which were secondary endpoints in the diabetes trials.)] | -4 | -1 | -3 | 23
Placebo | 121 | 1 | 1 | 1 | 0 | 1 | 0
Insulin Alone
Colesevelam hydrochloride 3.8 g | 46 | -3 | -12 | -5 | 0 | -3 | 19
Placebo | 48 | 2 | 4 | 2 | 3 | 2 | -2
Insulin in Combination with Oral Anti-diabetic Agents
Colesevelam hydrochloride 3.8 g | 83 | -4 | -13 | -4 | -1 | -3 | 25
Placebo | 73 | -1 | -3 | 0 | -1 | -1 | 2

16 HOW SUPPLIED/STORAGE AND HANDLING

Colesevelam hydrochloride 625 mg tablets are supplied as off-white, solid tablets imprinted with the word "Sankyo" and "C01" on one side and are available as follows:

- Bottles of 180 – NDC 0713-0936-81

Colesevelam hydrochloride 3.75 gram packets for oral suspension contain a white to pale yellow powder containing yellow granules and are available as follows:

- Cartons of 30 packets – NDC 0713-0935-30

STORAGE AND HANDLING

Store at 25°C (77°F); excursions permitted to 15-30°C (59-86°F) [see USP Controlled Room Temperature]. Protect from moisture. Brief exposure to 40°C (104°F) does not adversely affect colesevelam hydrochloride tablets.

17 PATIENT COUNSELING INFORMATION

Hypertriglyceridemia and Pancreatitis

Inform patients that colesevelam hydrochloride may increase their serum triglycerides which can lead to hypertriglyceridemia and pancreatitis. Instruct patients to discontinue colesevelam hydrochloride and seek prompt medical attention if the symptoms of acute pancreatitis occur (e.g., severe abdominal pain with or without nausea and vomiting) [see Warnings and Precautions (5.1)].

Gastrointestinal

Inform patients that colesevelam hydrochloride may cause bowel obstruction. Instruct patients to promptly discontinue colesevelam hydrochloride and seek medical attention if severe abdominal pain or severe constipation occurs [see Warnings and Precautions (5.2)].

Drug and Vitamin Interactions

Advise patients that colesevelam hydrochloride has drug interactions, and colesevelam hydrochloride may decrease the absorption of fat-soluble vitamins A, D, E, and K. Instruct patients to take oral vitamins at least 4 hours prior to colesevelam hydrochloride. Instruct patients to inform their physician about all the drugs and vitamins that they are prescribed or take over the counter [see Warnings and Precautions (5.3)and Drug Interactions (7)].

Hypertriglyceridemia and Cardiovascular Disease

Inform patients that colesevelam hydrochloride may increase serum triglycerides and that the long-term effect of hypertriglyceridemia on the risk of coronary artery disease is uncertain [see Warnings and Precautions (5.1)].

Administration [see Dosage and Administration (2.2, 2.4)]:

Tablets

Advise patients to take colesevelam hydrochloride tablets with a meal and liquid. Inform patients that colesevelam hydrochloride tablets can be taken as 6 tablets once daily or 3 tablets twice daily.

For Oral Suspension

Instruct patients to empty the entire contents of one packet into a glass or cup and add 1 cup (8 ounces) of water, fruit juice, or diet soft drinks. Stir well and drink. Advise patients to take colesevelam hydrochloride oral suspension with meals. Advise patient to not take colesevelam hydrochloride oral suspension in its dry form.

Females of Reproductive Potential

Advise females of reproductive potential that colesevelam hydrochloride may reduce the effectiveness of oral contraceptives, and to take oral contraceptives at least 4 hours before taking colesevelam hydrochloride [see Drug Interactions (7.1)and Use in Specific Populations (8.3)].

Marketed by:
Cosette Pharmaceuticals, Inc.
South Plainfield, NJ 07080

8-COLCP1 Iss. 03/2022

PRINCIPAL DISPLAY PANEL

NDC 0713-0936-81
Colesevelam Hydrochloride
Tablets
625 mg
180 Tablets

PRINCIPAL DISPLAY PANEL - 3.75 g Packet Label

TEAR HERE
No cutting required

Sugar-Free

This packet is contained within the
CARTON NDC 0713-0935-30
Rx only

Colesevelam
Hydrochloride
for Oral Suspension

3.75 g

Citrus Flavor
Single-Dose Packet

Each packet contains 3.75 grams of
colesevelam hydrochloride.

Keep Out of Reach of Children.
Package Not Child Resistant.

PRINCIPAL DISPLAY PANEL - 3.75 g Packet Carton

NDC 0713-0935-30
Rx only

30 packets

Colesevelam
Hydrochloride
for Oral Suspension

3.75 g

Each packet contains 3.75 grams of
colesevelam hydrochloride.

Dosing and use: see package insert.

Keep Out of Reach of Children.
Package Not Child Resistant.